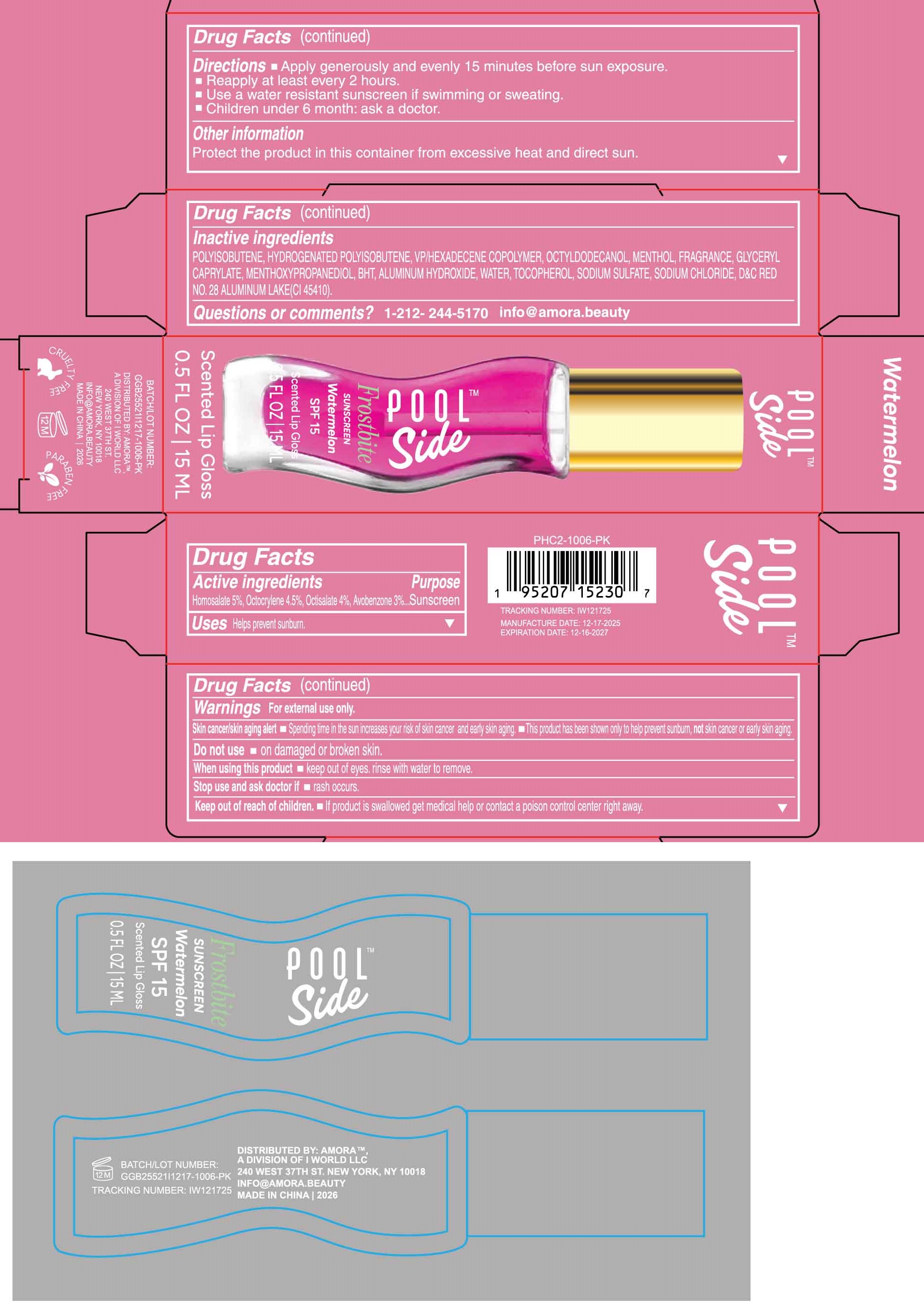 DRUG LABEL: Poolside Frostbite Sunscreen Watermelon SPF 15 Scented Lip Gloss
NDC: 85179-025 | Form: LIQUID
Manufacturer: I World LLC
Category: otc | Type: HUMAN OTC DRUG LABEL
Date: 20260116

ACTIVE INGREDIENTS: HOMOSALATE 50 mg/1 mL; OCTOCRYLENE 45 mg/1 mL; OCTISALATE 40 mg/1 mL; AVOBENZONE 30 mg/1 mL
INACTIVE INGREDIENTS: VINYLPYRROLIDONE/HEXADECENE COPOLYMER; OCTYLDODECANOL; MENTHOL; GLYCERYL MONOCAPRYLATE; 3-((L-MENTHYL)OXY)PROPANE-1,2-DIOL; BUTYLATED HYDROXYTOLUENE; ALUMINUM HYDROXIDE; WATER; TOCOPHEROL; SODIUM SULFATE; SODIUM CHLORIDE; D&C RED NO. 28

Poolside Frostbite Sunscreen Watermelon SPF 15 Scented Lip Gloss

Active ingredients

Homosalate 5%, Octocrylene 4.5%, Octisalate 4%, Avobenzone 3%

Purpose

Sunscreen

Uses

Helps prevent sunburn.

Warnings

For external use only.

Skin cancer/skin aging alert

- Spending time in the sun increases your risk of skin cancer and early skin aging.
- This product has been shown only to help prevent sunburn, not skin cancer or early skin aging.

Do not use

- on damaged or broken skin.

When using this product

- keep out of eyes. rinse with water to remove.

Stop use and ask doctor if

- rash occurs.

Keep out of reach of children.

- If product is swallowed get medical help or contact a poison control center right away.

Directions

- Apply generously and evenly 15 minutes before sun exposure.
- Reapply at least every 2 hours
- Use a water resistant sunscreen if swimming or sweating.
- Children under 6 month: ask a doctor.

Other information

Protect the product in this container from excessive heat and direct sun.

Inactive ingredients

POLYISOBUTENE, HYDROGENATED POLYISOBUTENE, VP/HEXADECENE COPOLYMER, OCTYLDODECANOL, MENTHOL, FRAGRANCE, GLYCERYL CAPRYLATE, MENTHOXYPROPANEDIOL, BHT, ALUMINUM HYDROXIDE, WATER, TOCOPHEROL, SODIUM SULFATE, SODIUM CHLORIDE, D&C RED NO.28 ALUMINUM LAKE (CI 45410).

Questions or comments?

1-212- 244-5170 info@amora.beauty